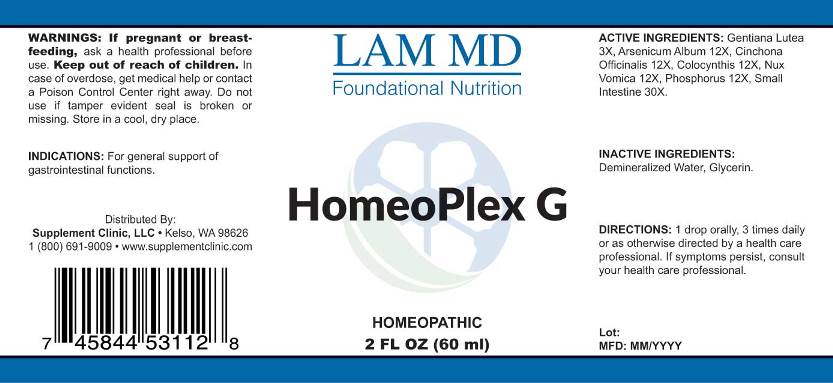 DRUG LABEL: Homeoplex G
NDC: 71781-0005 | Form: LIQUID
Manufacturer: Supplement Clinic, LLC.
Category: homeopathic | Type: HUMAN OTC DRUG LABEL
Date: 20171101

ACTIVE INGREDIENTS: GENTIANA LUTEA ROOT 3 [hp_X]/1 mL; ARSENIC TRIOXIDE 12 [hp_X]/1 mL; CINCHONA OFFICINALIS BARK 12 [hp_X]/1 mL; CITRULLUS COLOCYNTHIS FRUIT PULP 12 [hp_X]/1 mL; STRYCHNOS NUX-VOMICA SEED 12 [hp_X]/1 mL; PHOSPHORUS 12 [hp_X]/1 mL; PORK INTESTINE 30 [hp_X]/1 mL
INACTIVE INGREDIENTS: WATER; GLYCERIN

Drug Facts:

ACTIVE INGREDIENTS:

Gentiana Lutea 3X, Arsenicum Album 12X, Cinchona Officinalis 12X, Colocynthis 12X, Nux Vomica 12X, Phosphorus 12X, Small Intestine 30X.

INDICATIONS:

For general support of gastrointestinal functions.

WARNINGS:

If pregnant or breast-feeding, ask a health professional before use.
Keep out of reach of children. In case of overdose, get medical help or contact a Poison Control Center right away.
Do not use if tamper evident seal is broken or missing.
Store in cool, dry place.

Keep out of reach of children. In case of overdose, get medical help or contact a Poison Control Center right away.

DIRECTIONS:

1 drop orally, 3 times daily or as otherwise directed by a health care professional. If symptoms persist, consult your health care professional.

INDICATIONS:

For general support of gastrointestinal functions.

INACTIVE INGREDIENTS:

Demineralized Water, Glycerin

QUESTIONS:

Distributed By:
Supplement Clinic, LLC. • Kelso, WA 98626
1(800)691-9009 • www.supplementclinic.com

PACKAGE LABEL DISPLAY:

LAM MD
Foundational Nutrition

HomeoPlex G

HOMEOPATHIC
2 FL OZ (60 ml)